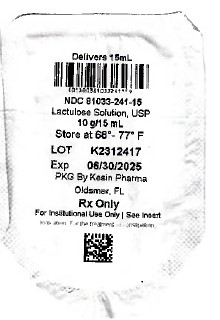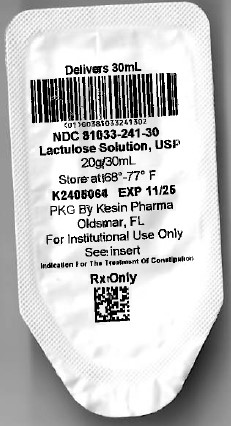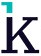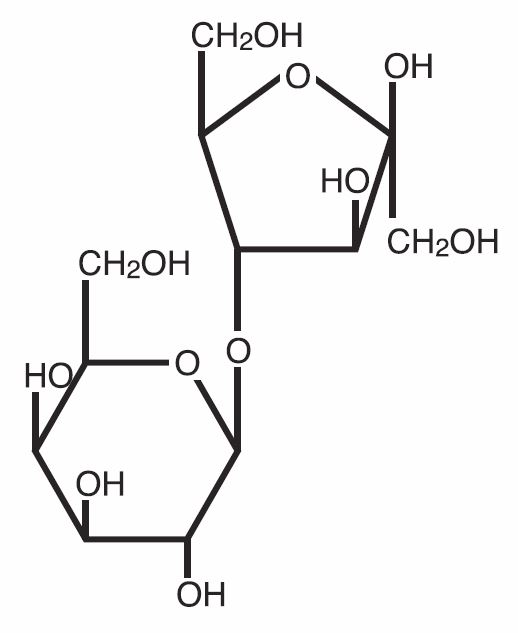 DRUG LABEL: Lactulose Solution
NDC: 81033-241 | Form: SOLUTION
Manufacturer: Kesin Pharma Corporation
Category: prescription | Type: HUMAN PRESCRIPTION DRUG LABEL
Date: 20241203

ACTIVE INGREDIENTS: LACTULOSE 10 g/15 mL
INACTIVE INGREDIENTS: FD&C YELLOW NO. 6; D&C YELLOW NO. 10; WATER

HIGHLIGHTS OF PRESCRIBING INFORMATION

"These highlights do not include all the information needed to use" "see full prescribing information for" and "Initial U.S. Approval" Lactulose Solution USP, 10 g/15 mL

RECENT MAJOR CHANGES

DESCRIPTION 10/2024

INDICATIONS AND USAGE 10/2024

HOW SUPPLIED 10/2024

FULL PRESCRIBING INFORMATION

DESCRIPTION

Lactulose is a synthetic disaccharide in solution form for oral administration. Each 15mL contains: Lactulose 10g (less than 1.6g galactose, less than 1.2g lactose, and 0.1g or less of fructose). It also contains D&C Yellow No. 10, FD & C Yellow No. 6 and Purified Water.
Lactulose is a colonic acidifier which promotes laxation.
The chemical name for lactulose is 4-0-ß-D-galactopyranos-D-fructofuranose. It has the following structural formula:

The molecular weight is 342.30. It is freely soluble in water.

CLINICAL PHARMACOLOGY

Lactulose is poorly absorbed from the gastrointestinal tract, and no enzyme capable of hydrolysis of this disaccharide is present in human gastrointestinal tissue. As a result, oral doses of lactulose solution reach the colon virtually unchanged. In the colon, lactulose is broken down primarily to lactic acid, and also to small amounts of formic and acetic acids, by the action of colonic bacteria, which results in an increase in osmotic pressure and slight acidification of the colonic contents. This in turn causes an increase in stool water content and softens the stool.
Since lactulose does not exert its effect until it reaches the colon, and since transit time through the colon may be slow, 24 to 48 hours may be required to produce the desired bowel movement.
Lactulose solution given orally to man and experimental animals resulted in only small amounts reaching the blood.
Urinary excretion has been determined to be 3% or less and is essentially complete within 24 hours.

INDICATIONS AND USAGE

For the treatment of constipation. In patients with a history of chronic constipation, lactulose solution therapy increases the number of bowel movements per day and the number of days on which bowel movements occur.

CONTRAINDICATIONS

Since lactulose solution contains galactose (less than 1.6 g/15 mL), it is contraindicated in patients who require a low galactose diet.

WARNINGS

A theoretical hazard may exist for patients being treated with lactulose solution who may be required to undergo electrocautery procedures during proctoscopy or colonoscopy. Accumulation of H2 gas in significant concentration in the presence of an electrical spark may result in an explosive reaction. Although this complication has not been reported with lactulose, patients on lactulose therapy undergoing such procedures should have a thorough bowel cleansing with a non-fermentable solution. Insufflation of CO2 as an additional safeguard may be pursued but is considered to be a redundant measure.

PRECAUTIONS

General
Since lactulose solution contains galactose (less than1.6 g/15 mL) and lactose (less than 1.2 g/15 mL), it should be used with caution in diabetics. Infants receiving lactulose may develop hyponatremia and dehydration.

Drug Interactions

There have been conflicting reports about the concomitant use of neomycin and lactulose solution. Theoretically, the elimination of certain colonic bacteria by neomycin and possibly other anti-infective agents may interfere with the desired degradation of lactulose and thus prevent the acidification of colonic contents. Thus the status of the lactulose-treated patient should be closely monitored in the event of concomitant oral anti-infective therapy.
Results of preliminary studies in humans and rats suggest that nonabsorbable antacids given concurrently with lactulose may inhibit the desired lactulose-induced drop in colonic pH. Therefore, a possible lack of desired effect of treatment should be taken into consideration before such drugs are given concomitantly with lactulose.

Carcinogenesis, Mutagenesis, and Impairment of Fertility

There are no known human data on log-term potential for carcinogenicity, mutagenicity, or impairment of fertility.

There are no known animal data on long-term potential for mutagenicity.

Administration of lactulose solution in the diet of mice for 18 months in concentrations of 3 and 10 percent (v/w) did not produce any evidence of carcinogenicity.
In studies of mice, rats, and rabbits, doses of lactulose solution up to 6 or 12 mL/kg/day produced no deleterious effects in breeding, conception, or parturition.

Pregnancy: Teratogenic Effects; Pregnancy Category B.

Reproduction studies have been performed in mice, rats, and rabbits at doses up to 2 or 4 times the usual human oral dose and have revealed no evidence of impaired fertility or harm to the fetus due to lactulose. There are, however, no adequate and well-controlled studies in pregnant women. Because animal reproduction studies are not always predictive of human response, this drug should be used during pregnancy only if clearly needed.

Nursing Mothers

It is not known whether this drug is excreted in human milk. Because many drugs are excreted in human milk, caution should be exercised when lactulose is administered to a nursing woman.

Pediatric Use

Very little information on the use of lactulose in pediatric patients has been recorded (see DOSAGE AND ADMINISTRATION).

ADVERSE REACTIONS

Precise frequency data are not available. Lactulose may produce gaseous distention with flatulence or belching and abdominal discomfort such as cramping in about 20% of patients. Excessive dosage can lead to diarrhea with potential complications such as loss of fluids, hypokalemia, and hypernatremia. Nausea and vomiting have been reported.
To report SUSPECTED ADVERSE REACTIONS, contact Kesin Pharma at 1-833-537-4679 or FDA at 1-800-FDA-1088 or www.fda.gov/medwatch.

OVERDOSAGE

Signs and Symptoms

There have been no reports of accidental overdosage. In the event of overdosage, it is expected that diarrhea and abdominal cramps would be the major symptoms. Medication should be terminated.

Oral LD50

The acute oral LD50 of the drug is 48.8 mL/kg in mice and greater than 30 mL/kg in rats.

Dialysis

Dialysis data are not available for lactulose. Its molecular similarity to sucrose, however, would suggest that it should be dialyzable.

DOSAGE AND ADMINISTRATION

Adult
The usual adult oral dosage is 2 to 3 tablespoonfuls (30 to 45 mL, containing 20 g to 30 g of lactulose) three or four times daily. The dosage may be adjusted every day or two to produce 2 or 3 soft stools daily.

Pediatric

Very little information on the use of lactulose in young children and adolescents has been recorded. As with adults, the subjective goal in proper treatment is to produce 2 to 3 soft stools daily. On the basis of information available, the recommended initial daily oral dose in infants is 2.5 to 10 mL in divided doses. For older children and adolescents, the total daily dose is 40 to 90 mL. If the initial dose causes diarrhea, the dose should be reduced immediately. If diarrhea persists, lactulose should be discontinued.
Note: Some patients have found that lactulose solution may be more acceptable when mixed with fruit juice, water or milk.

HOW SUPPLIED

Lactulose Solution, USP, 10 g/15 mL is a clear, yellow to golden-yellow solution supplied as follows:
NDC: 81033-241-15 - 15 mL Unit Dose Cup
NDC: 81033-241-50 - Case containing 100 (15mL unit dose cups)
NDC: 81033-241-30 - 30 mL Unit Dose Cup
NDC: 81033-241-51 - Case containing 100 (30mL unit dose cups)

STORAGE

Store at 20° to 25°C (68° to 77°F) [See USP Controlled Room Temperature]. Do not freeze. Keep tightly closed.
Under recommended storage conditions, a normal darkening of color may occur. Such darkening is characteristic of sugar solutions and does not affect therapeutic action.

Prolonged exposure to temperatures above 86°F (30°C) or to direct light may cause extreme darkening and turbidity which may be pharmaceutically objectionable. If this condition develops, do not use. Prolonged exposure to freezing temperatures may cause change to a semisolid, too viscous to pour. Viscosity will return to normal upon warming to room temperature.
Dispense in a tight, light-resistant container as defined in the USP, with a child-resistant closure.

Packaged by:
Kesin Pharma
Oldsmar FL, 34677
PI Rev. 10/2024

PACKAGE LABEL

Delivers 15ml

NDC 81033-241-15

LACTULOSE SOLUTION, USP 10 g/15 mL

FOR ORAL OR RECTAL ADMINISTRATION

Store at 20-25°C (68-77°F)

PKG By Kesin Pharma

Oldsmar, FL

Rx Only

For Institutional Use Only| See Insert

Delivers 30ml

NDC 81033-241-30

LACTULOSE SOLUTION, USP 20 g/35 mL

FOR ORAL OR RECTAL ADMINISTRATION

Store at 20-25°C (68-77°F)

PKG By Kesin Pharma

Oldsmar, FL

Rx Only

For Institutional Use Only

See Insert